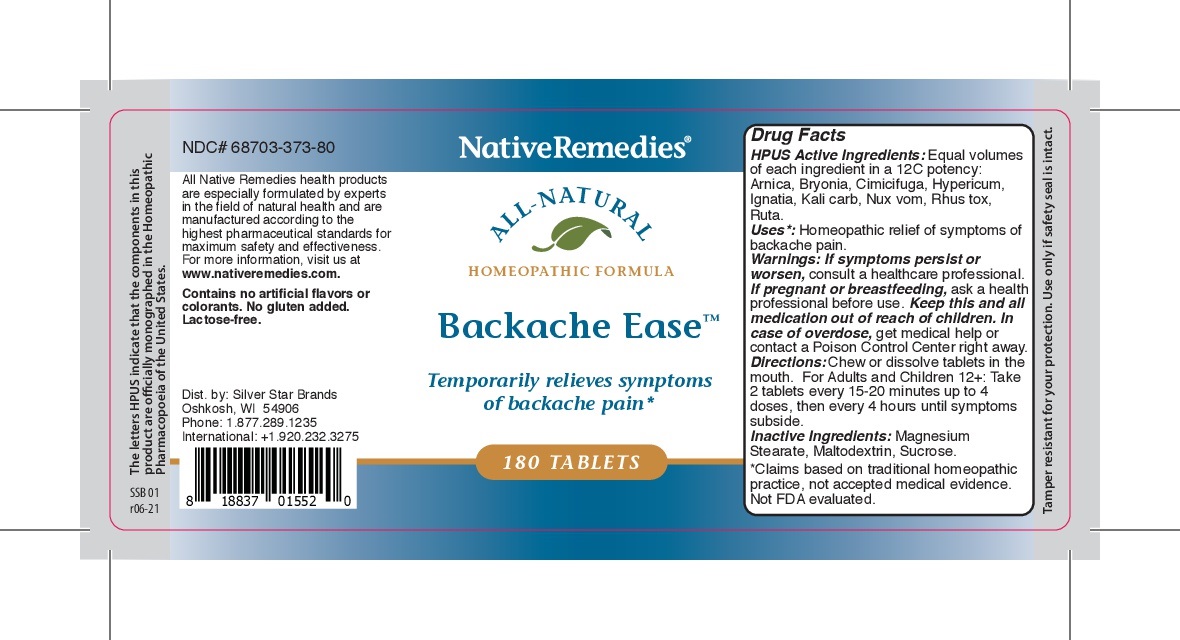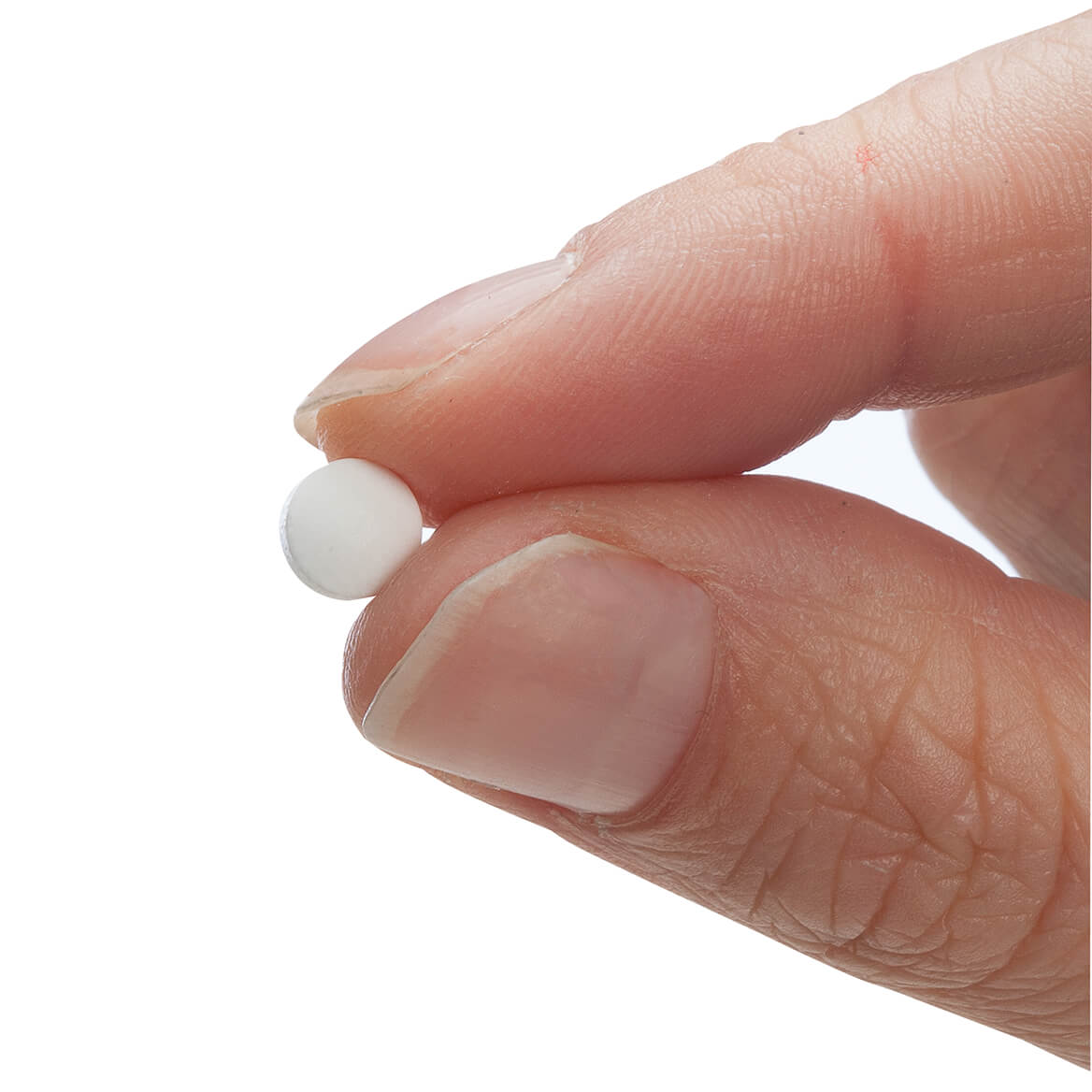 DRUG LABEL: NativeRemedies Backache Ease
NDC: 68703-373 | Form: TABLET
Manufacturer: Silver Star Brands
Category: homeopathic | Type: HUMAN OTC DRUG LABEL
Date: 20250101

ACTIVE INGREDIENTS: RUTA GRAVEOLENS FLOWERING TOP 12 [hp_C]/180 1; HYPERICUM PERFORATUM 12 [hp_C]/180 1; STRYCHNOS NUX-VOMICA SEED 12 [hp_C]/180 1; ARNICA ANGUSTIFOLIA FLOWER 12 [hp_C]/180 1; BRYONIA ALBA ROOT 12 [hp_C]/180 1; POTASSIUM CARBONATE 12 [hp_C]/180 1; STRYCHNOS IGNATII SEED 12 [hp_C]/180 1; ACTAEA CIMICIFUGA ROOT 12 [hp_C]/180 1; TOXICODENDRON RADICANS LEAF 12 [hp_C]/180 1
INACTIVE INGREDIENTS: SUCROSE; MAGNESIUM STEARATE; MALTODEXTRIN

NativeRemedies® Backache Ease Tablets

HPUS Active Ingredients: Equal volumes of each ingredient in a 12C potency: Arnica, Bryonia, Cimicifuga, Hypericum, Ignatia, Kali carb, nux vom, rhus tox, ruta.

Uses*:

Uses*: Homeopathic relief of symptoms of backache pain.

*Claims based on traditional homeopathic practice, not accepted medical evidence. Not FDA evaluated.

Warnings

Warnings: If symptoms persist or worsen, consult a healthcare professional. If pregnant or breastfeeding, ask a healthcare professional before use. keep this and all medication out of reach of children. In case of overdose, get medical help or contacta Poison Control Center right away.

Directions:

Directions: chew or dissolve tablets in the mouth. For Adults and Children 12+: Take 2 tablets every 15-20 minutes up to 4 doses, then every 4 hours until symptoms subside.

OTHER SAFETY INFORMATION

Contains no artificial flavors or colorants. No gluten added. Lactose Free.

Tamper resistsant for your protection. use only if saftey seal is intact.

Inactive Ingredients:

Inactive Ingredients: Magnesium Stearate, Maltodextrin, Sucrose.

KEEP OUT OF REACH OF CHILDREN

Keep this and all medication out of reach of children.

PREGNANCY OR BREAST FEEDING

If pregnant or breastfeeding, ask a health professional before use.

PURPOSE

Temporarily relieves symptoms of backache pain.*

*claims based on traditional homeopathic practice, not accepted medical evidence. Not FDA evaluated.